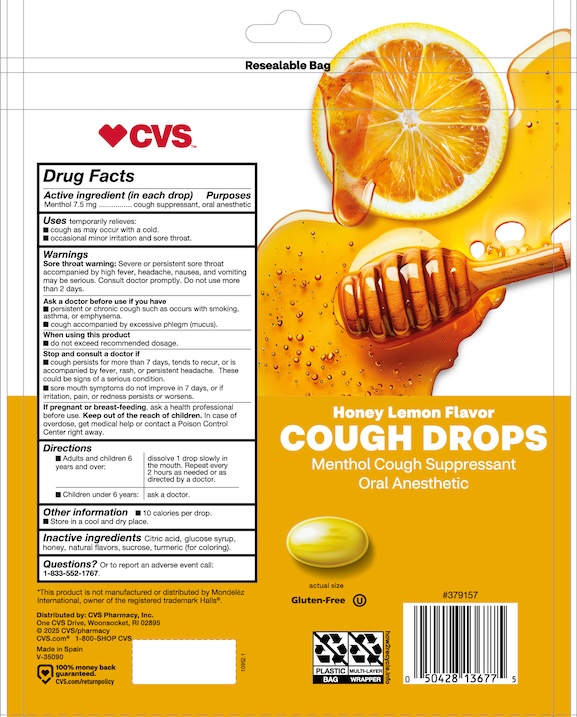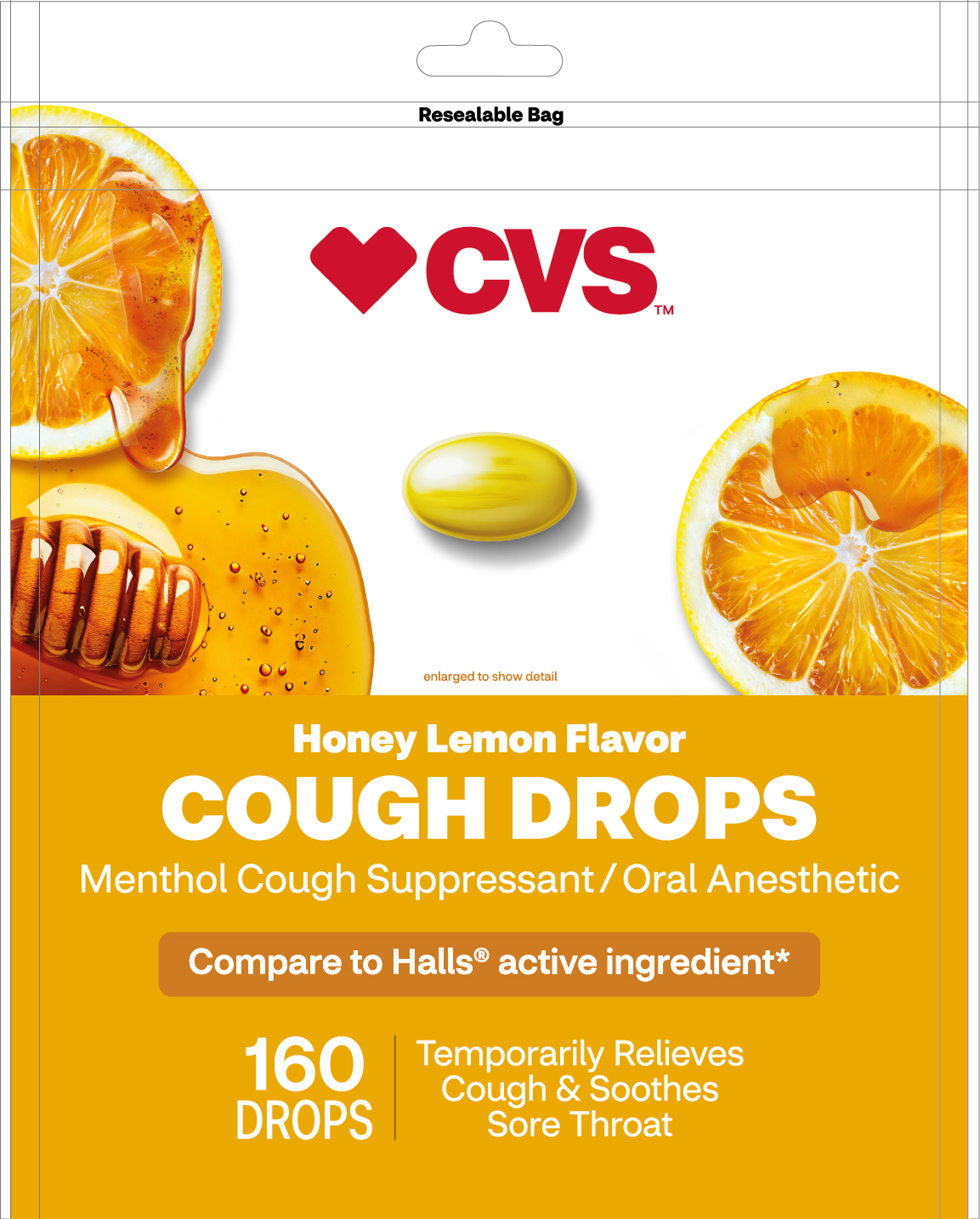 DRUG LABEL: Menthol Cough Drops Honey Lemon Flavor
NDC: 51316-987 | Form: PASTILLE
Manufacturer: CVS Pharmacy
Category: otc | Type: HUMAN OTC DRUG LABEL
Date: 20250913

ACTIVE INGREDIENTS: MENTHOL 7.5 mg/1 1
INACTIVE INGREDIENTS: CITRIC ACID MONOHYDRATE; CORN SYRUP; HONEY; FLAVONE; TURMERIC; SUCROSE

Sugar Free Menthol Cough Drops

Active Ingredient:

- Menthol 7.5 mg.............cough suppresant/ oral anesthetic

PURPOSE

Uses temporarily relieves:

- cough as may occur with a cold
- ocassional minor irritation and sore throat

INDICATIONS AND USAGE

Uses temporarily relieves:

cough as may occur with a cold
ocassional minor irritation and sore throat

Warnings

Sore throat warning: severe or persistence sore throat accompanied by high fever, headache, nausea and vomiting may be serious. Consult a doctor promptly. Do not use more than 2 days.

Stop and consult a doctor before use if

- cough persist for more than 7 days, tends to recur, or is accompanied by fever, rash, or persistent headache. These could be signs of a serious condition.
- sore mouth symptoms do not improve in 7 days, or if irritation, pain or redness persists or worsens.

Stop and consult a doctor before use if

- cough persist for more than 7 days, tends to recur, or is accompanied by fever, rash, or persistent headache. These could be signs of a serious condition.
- sore mouth symptoms do not improve in 7 days, or if irritation, pain or redness persists or worsens.

PREGNANCY OR BREAST FEEDING

If pregnant or breast-feeding, ask a health professional before use.

KEEP OUT OF REACH OF CHILDREN

Keep this and all drugs out of the reach of children.

OVERDOSAGE

In case of accidental overdose, get medical help or contact a Poison Control Center right away.

Directions

- Adults and children 6 years and over: dissolve 1 drop slowly in the mouth. Repeated every 2 hours as needed or as directed by a doctor.
- Children under 6 years: as a doctor

OTHER SAFETY INFORMATION

- 10 calories per drop
- Store in a cool and dry place

INACTIVE INGREDIENT

citric acid, glucose syrup, honey, natural flavors, sucrose, turmeric (for coloring)

QUESTIONS

Questions? or to report and adverse event call: 1-833-552-1767

- Directions
- Stop and consult a doctor
- Warning